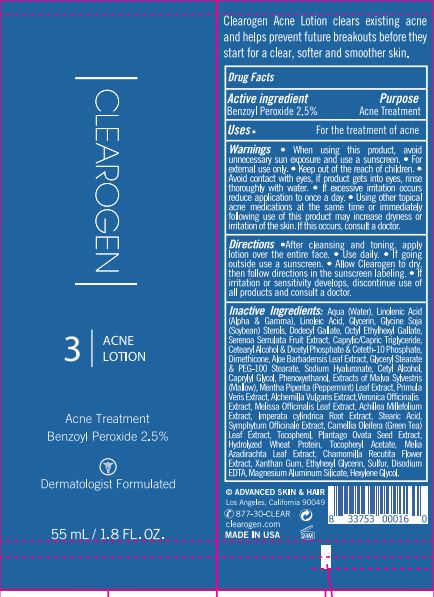 DRUG LABEL: CLEAROGEN 3
NDC: 62742-4238 | Form: LOTION
Manufacturer: Allure Labs
Category: otc | Type: HUMAN OTC DRUG LABEL
Date: 20231206

ACTIVE INGREDIENTS: BENZOYL PEROXIDE 2.5 g/100 g
INACTIVE INGREDIENTS: GLYCERYL MONOSTEARATE; GLYCERIN; DIMETHICONE; PLANTAGO OVATA SEED; WATER; DIHEXADECYL PHOSPHATE; PHENOXYETHANOL; STEARIC ACID; .ALPHA.-TOCOPHEROL ACETATE; CETYL ALCOHOL; CAPRYLYL GLYCOL; PRIMULA VERIS; ALCHEMILLA XANTHOCHLORA FLOWERING TOP; XANTHAN GUM; VERONICA OFFICINALIS FLOWERING TOP; COMFREY ROOT; CAMELLIA OLEIFERA LEAF; MAGNESIUM ALUMINUM SILICATE; HEXYLENE GLYCOL; ETHYLHEXYL GALLATE; CETETH-10 PHOSPHATE; ALOE VERA LEAF; MELISSA OFFICINALIS LEAF; HYDROLYZED WHEAT PROTEIN (ENZYMATIC, 3000 MW); ETHYLHEXYLGLYCERIN; ACHILLEA MILLEFOLIUM; IMPERATA CYLINDRICA ROOT; AZADIRACHTA INDICA LEAF; CHAMOMILE; SULFUR; LINOLENIC ACID; DODECYL GALLATE; SAW PALMETTO; SOY STEROL; MEDIUM-CHAIN TRIGLYCERIDES; CETOSTEARYL ALCOHOL; PEG-100 STEARATE; LINOLEIC ACID; HYALURONATE SODIUM; EDETATE DISODIUM ANHYDROUS; MALVA SYLVESTRIS FLOWERING TOP; MENTHA PIPERITA LEAF; TOCOPHEROL

Drug Facts

Active ingredient

Benzoyl Peroxide 2.5%

Purpose- Acne Treatment

INDICATIONS AND USAGE

Uses. For the treatment of acne

WARNINGS

Warning : For external use only

Avoid unnecessary sun exposure and use sunscreen.

WHEN USING

Avoid contact with eye, If product gets into eyes, rinse thoroughly with water.

STOP USE

If excessive irritation occurs reduce application to once a day. Using other topical acne medication at the same time or immediately following use of this product may increase dryness or irritation of the skin. If this occurs, consult a doctor.

Keep out of reach of children.

DOSAGE AND ADMINISTRATION

Direction:

After cleansing and toning apply lotion over the entire face. Use daily. If going outside use a sunscreen

Allow Clearogen to dry then follow directions in the sunscreen labeling. If irritation or sensitivity develops, discontinue use of all products, and consult a doctor.

OTHER SAFETY INFORMATION

Not applicable

Inactive Ingredient:

Aqua (Water), Linolenic Acid (Alpha & Gamma), Linoleic Acid,Glycerin, Glycine Soja (Soyabean) Sterols, Dodecyl Gallate, Octyl Ethylhexyl Gallate, Serenoa Serrulata Fruit Extract, Caprylic/Capric Triglyceride, Cetearyl Alcohol & Dicetyl Phosphate & Ceteth-10 Phosphate, Dimethicone, Aloe Barbadensis Leaf Extract, Glyceryl Stearate & PEG-100 Stearate, Sodium Hyaluronate, Cetyl Alcohol, Caprylyl Glycol, Phenoxyethanol,Extract of Malva Sylvestris (Mallow), Mentha Piperita (Peppermint) Leaf Extract, Primula Veris Extract, Alchemilla Vulgaris Extract, Veronica Officinalis Extract, Melissa Officinalis Leaf Extract, Achillea Millefolium Extract, Imperata Cylindrica Root Extract, Stearic Acid, Symphytum Officinale Extract, Camellia Oleifera(Green Tea)Leaf Exact, Tocopherol, Plantago Ovata Seed Extract, Hydrolyzed Wheat Protein, Tocopheryl Acetate, Melia Azadirachta Leaf Extract, Chamomilla Recutita Flower Exact, Xanthan Gum, Ethylhexyl glycerin, Sulfur, Disodium EDTA, Magnesium Aluminum Silicate, Hexylene Glycol.